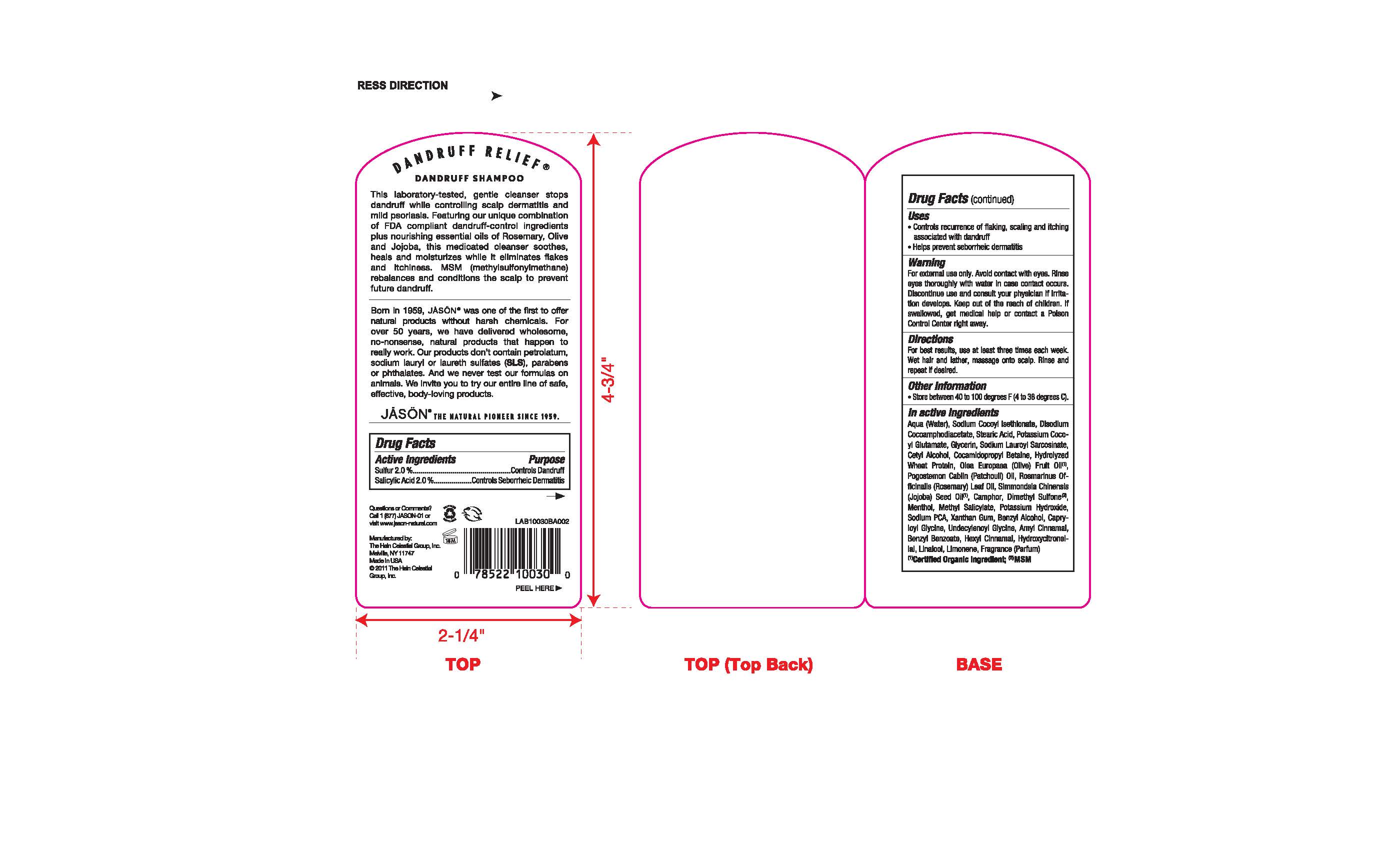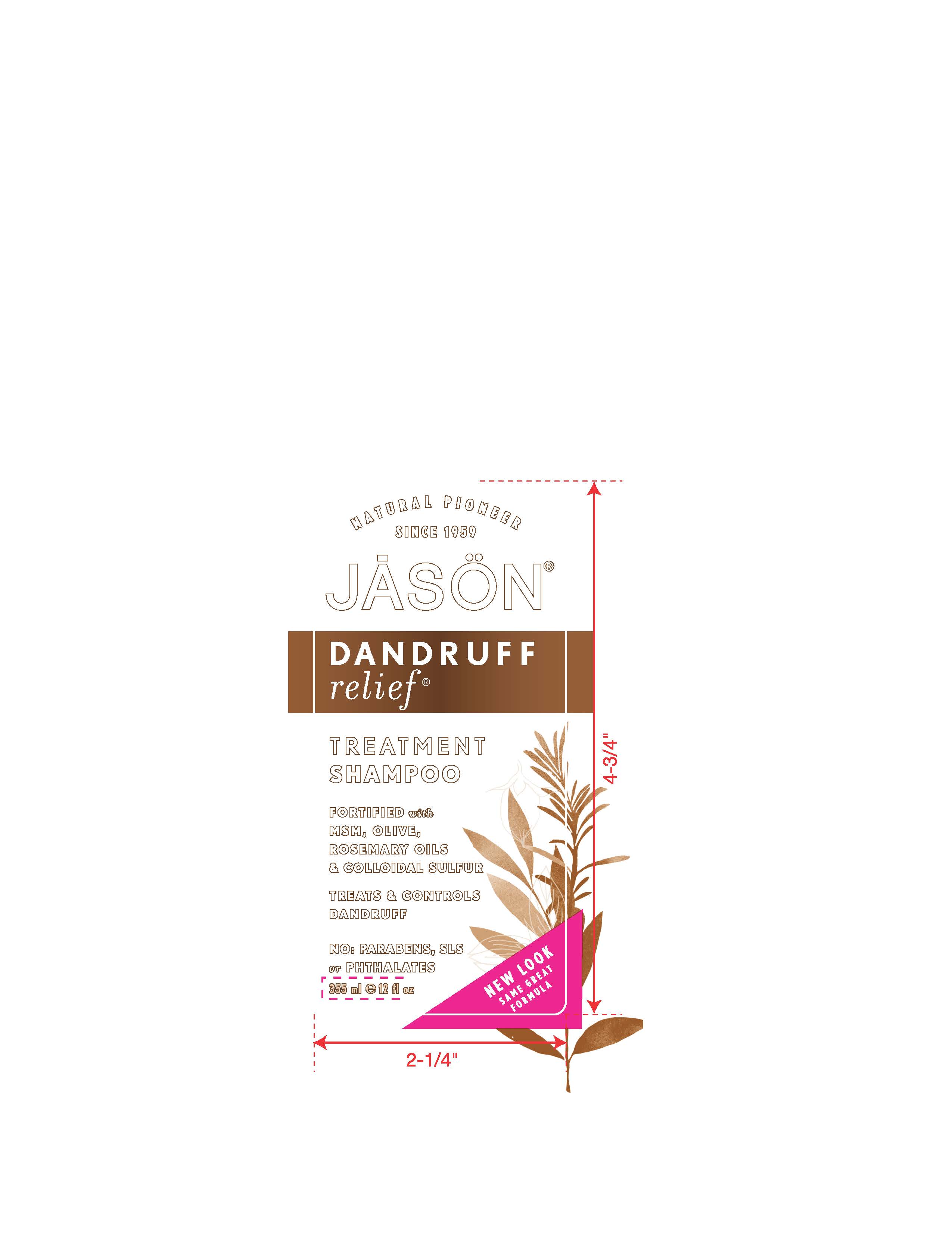 DRUG LABEL: Jason Dandruff Relief Treatment
NDC: 61995-0302 | Form: SHAMPOO
Manufacturer: The Hain Celestial Group, Inc
Category: otc | Type: HUMAN OTC DRUG LABEL
Date: 20120612

ACTIVE INGREDIENTS: SULFUR 2.0 g/100 g; SALICYLIC ACID  2.0 g/100 g
INACTIVE INGREDIENTS: WATER ; SODIUM COCOYL ISETHIONATE ; DISODIUM COCOAMPHODIACETATE ; STEARIC ACID; GLYCERIN ; SODIUM LAUROYL SARCOSINATE; CETYL ALCOHOL; COCAMIDOPROPYL BETAINE; HYDROLYZED WHEAT PROTEIN (ENZYMATIC, 3000 MW); OLIVE OIL ; PATCHOULI OIL; ROSEMARY OIL; JOJOBA OIL; CAMPHOR (NATURAL) ; DIMETHYL SULFONE ; MENTHOL; METHYL SALICYLATE ; POTASSIUM HYDROXIDE ; SODIUM PYRROLIDONE CARBOXYLATE ; XANTHAN GUM ; BENZYL ALCOHOL; CAPRYLOYL GLYCINE ; UNDECYLENOYL GLYCINE; .ALPHA.-AMYLCINNAMALDEHYDE ; BENZYL BENZOATE ; .ALPHA.-HEXYLCINNAMALDEHYDE ; HYDROXYCITRONELLAL; LINALOOL, (+/-)-; LIMONENE, (+)- 

Drug Facts

ACTIVE INGREDIENT

Sulfur 2.0%

Salicylic Acid 2.0%

PURPOSE

Sulfur 2.0% Controls Dandruff

Salicylic Acid 2.0% Controls Seborrheic Dermatitis

INDICATIONS AND USAGE

- Controls recurrence of flaking, scaling and itching associated with dandruff
- Helps prevent seborrheic dermatitis

WARNINGS

For external use only. Avoid contact with eyes.Rinse eyes throughly with water in case contact occurs.Discontinue use and consult your physician if irritation develops.

Keep out of reach of children. If swallowed get medical help or contact Poison Center right away.

DOSAGE AND ADMINISTRATION

For best results, use at least three times each week. Wet hair and lather,massage into scalp. Rinse and repeat if desired. Store between 40 to 100 degrees F (4 to 38 degrees C).

INACTIVE INGREDIENT

Aqua (Water), Sodium Cocoyl Isothionate, Disodium Cocoamphodiacetate, Stearic Acid,Potassium Cocoyl Glutamate, Glycerin, Sodium Lauroyl Sarcosinate, Cetyl Alcohol, Olea Europaea (Olive) Fruit Oil (1), Pogostemon Cablin (Patchouli) Oil, Rosmarinus Officinalis (Rosemary) Leaf Oil, Simmondsia Chinensis (Jojoba) Seed Oil (1), Camphor, Dimethyl Sulfone (2), Menthol, Methyl Salicylate, Potassium Hydroxide, Sodium PCA, Xanthan Gum, Benzyl Alcohol, Capryloyl Glycine, Undecylenoyl Glycine, Amyl Cinnamal, Benzyl Benzoate, Hexyl Cinnamal, Hydroxycitronellal, Linalool, Limonene, Fragrance (Parfum)

(1) Certified Organic Ingredients
(2) MSM

QUESTIONS

Questions? Visit www.jason-natural.com or call 1-877-527-Jason-01weekdays from 7am-5pm MST.